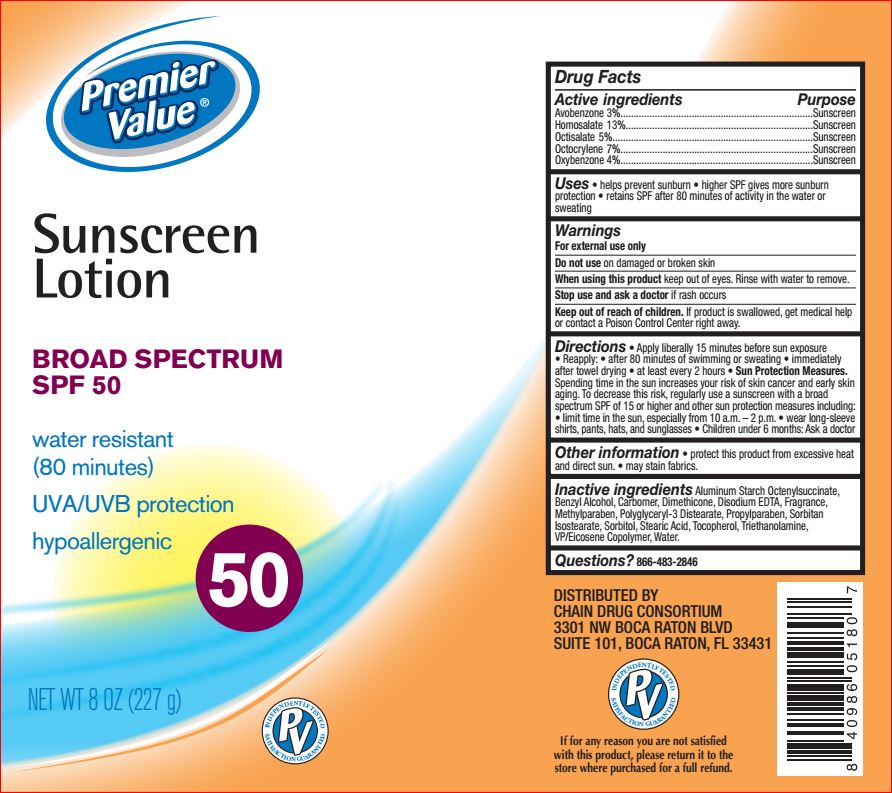 DRUG LABEL: Sunscreen SPF 50
NDC: 68016-270 | Form: LOTION
Manufacturer: Premier Value
Category: otc | Type: HUMAN OTC DRUG LABEL
Date: 20180810

ACTIVE INGREDIENTS: AVOBENZONE 3 g/100 g; HOMOSALATE 13 g/100 g; OCTISALATE 5 g/100 g; OCTOCRYLENE 7 g/100 g; OXYBENZONE 4 g/100 g
INACTIVE INGREDIENTS: ALUMINUM STARCH OCTENYLSUCCINATE; BENZYL ALCOHOL; CARBOMER HOMOPOLYMER TYPE C (ALLYL PENTAERYTHRITOL CROSSLINKED); DIMETHICONE; EDETATE DISODIUM; METHYLPARABEN; POLYGLYCERYL-3 DISTEARATE; PROPYLPARABEN; SORBITAN ISOSTEARATE; SORBITOL; STEARIC ACID; TOCOPHEROL; TROLAMINE; EICOSYL POVIDONE; WATER

Drug Facts

Active Ingredients

3% Avobenzone

13% Homosalate

5% Octisalate

7% Octocrylene

4% Oxybenzone

Purpose

Sunscreen

Uses

- helps prevent sunburn • If used as directed with other
  sun protection measures (see Directions), decreases the risk of
  skin cancer and early skin aging caused by sun.

Warnings

For external use only

Do not use

on damaged or broken skin

When using this product

keep out of eyes. Rinse with water to remove.

Stop use and ask a doctor

if rash occurs

Keep out of reach of children.

If product is swallowed, get medical help or contact a Poison Control Center right away.

Directions

- apply liberally 15 minutes before sun exposure
- reapply: after 80 minutes of swimming or sweating, immediately after towel drying, at least every 2 hours
- Sun Protection Measures. Spending time in the sun increases your risk of skin cancer and early skin aging. To decrease this risk, regularly use a sunscreen with a broad spectrum SPF of 15 or higher and other sun protection measures including:
- limit time in the sun, especially from 10 a.m. - 2 p.m.
- wear long-sleeve shirts, pants, hats, and sunglasses
- children under 6 months: Ask a doctor

Inactive Ingredients

Aluminum Starch Octenylsuccinate, Benzyl Alcohol, Carbomer, Dimethicone, Disodium EDTA, Fragrance, Methylparaben, Polyglyceryl-3 Distearate, Propylparaben, Sorbitan Isostearate, Sorbitol, Stearic Acid, Tocopherol, Triethanolamine, VP/Eicosene Copolymer, Water

Other Information

- protect this product from excessive heat and direct sun
- may stain fabrics